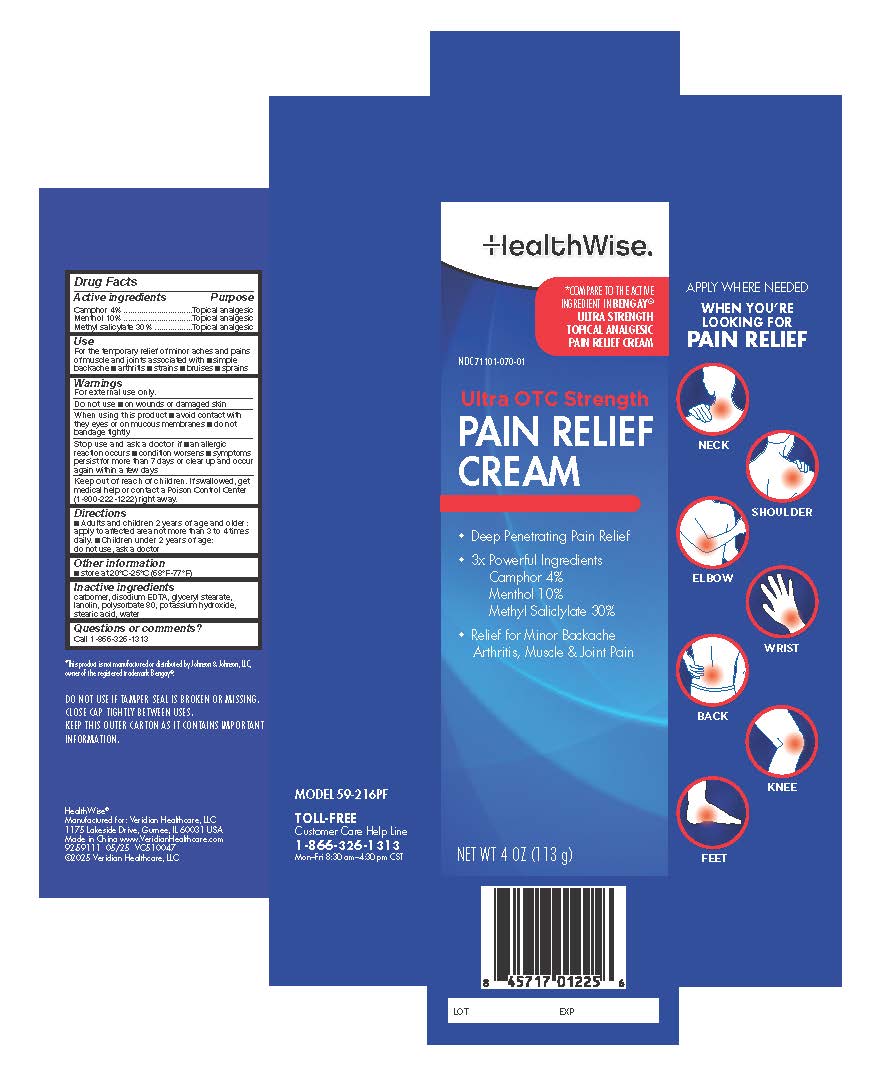 DRUG LABEL: HealthWise Ultra OTC Strength Pain Relief Cream
NDC: 71101-070 | Form: CREAM
Manufacturer: Veridian Healthcare
Category: otc | Type: HUMAN OTC DRUG LABEL
Date: 20250604

ACTIVE INGREDIENTS: CAMPHOR (NATURAL) 40 mg/1 g; MENTHOL, UNSPECIFIED FORM 100 mg/1 g; METHYL SALICYLATE 300 mg/1 g
INACTIVE INGREDIENTS: CARBOMER INTERPOLYMER TYPE A (55000 CPS); GLYCERYL 1-STEARATE; LANOLIN; POLYSORBATE 80; POTASSIUM HYDROXIDE; EDETATE DISODIUM ANHYDROUS; WATER; STEARIC ACID

HealthWise Ultra OTC Strength Pain Relief Cream

Drug Facts

ACTIVE INGREDIENT

Methyl Salicylate 30%

Menthol 10%

Camphor 4%

Active ingredients | Purpose
Camphor 4% | Topical analgesic
Menthol 10% | Topical analgesic
Methyl salicylate 30% | Topical analgesic

Use

For the temporary relief of minor aches and pains of muscle and joints associated with ■ simple backache ■ arthritis ■ strains ■ bruises ■ sprains

Warnings

For external use only.

Do not use

- than otherwise directed
- on wounds or damaged skin
- a bandage tightly

Stop use and ask a physician if

- rash or excessive irritation of the skin develops
- condition worsens or symptoms persist for more than 7 days
- condition clears up and occurs again within a few days

PREGNANCY OR BREAST FEEDING

If pregnant or breast-feeding,ask a health professional before use.

Keep out of reach of children.If swallowed, get medical help or contact a Poison Control Center right away: 800-222-1222.

Directions

Adults and children 2 years of age and older:

- apply to affected area no more than 3 to 4 times daily

Children under 2 years of age:

- do not use, ask a doctor

Other information

- store at 20°C -25°C(68 to 77°F)

Inactive ingredients

carbomer, disodium EDTA, glyceryl stearate, lanolin, polysorbate 80, potassium hydroxide, stearic acid, water

Questions or comments?

1-866-323-1313